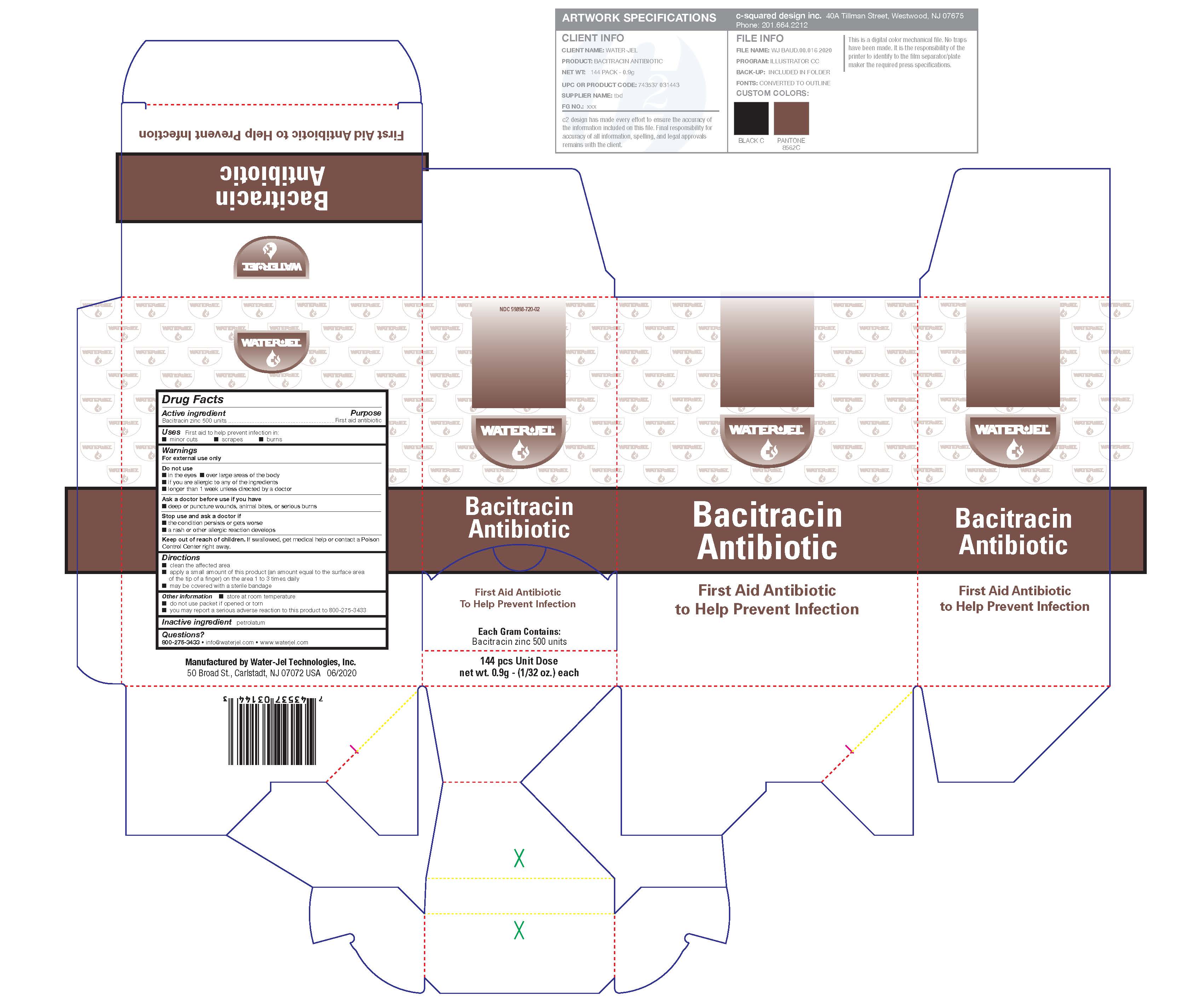 DRUG LABEL: Bacitracin
NDC: 59898-720 | Form: OINTMENT
Manufacturer: Water-Jel Technologies
Category: otc | Type: HUMAN OTC DRUG LABEL
Date: 20250106

ACTIVE INGREDIENTS: BACITRACIN ZINC 500 [iU]/1 g
INACTIVE INGREDIENTS: PETROLATUM

Bacitracin Antibiotic

Active ingredient

Bacitracin zinc 500 units

Purpose

First aid antibiotic

Uses

first aid to help prevent infection in

- minor cuts
- scrapes
- burns

Warnings

For external use only

Do not use

- in the eyes or over large areas of the body
- if you are allergic to any of the ingredients
- longer than 1 week unless directed by a doctor

Ask a doctor before use if you have

- a deep or puncture wounds, animal bites or serious burns

Stop use and ask a doctor if

- the condition persists or gets worse
- a rash or other allergic reaction develops

Keep out of the reach of children

If swallowed, get medical help or contact a Poison Control Center right away.

Directions

- clean the affected area
- apply a small amount of the product (an amount equal to the surface area of the tip of a finger) on the area 1 to 3 times daily
- may be covered with a sterile bandage

Other information

- store at room temperature
- do not use any opened or torn packets
- you may report a serious adverse reaction to this product to 800-275-3433

Inactive ingredient

petrolatum

Questions or comments?

1-800-276-3433 info@waterjel.com www.waterjel.com
Manufactured by Water-Jel Technologies, Inc

50 Broad St., Carlstadt NJ 07072 USA